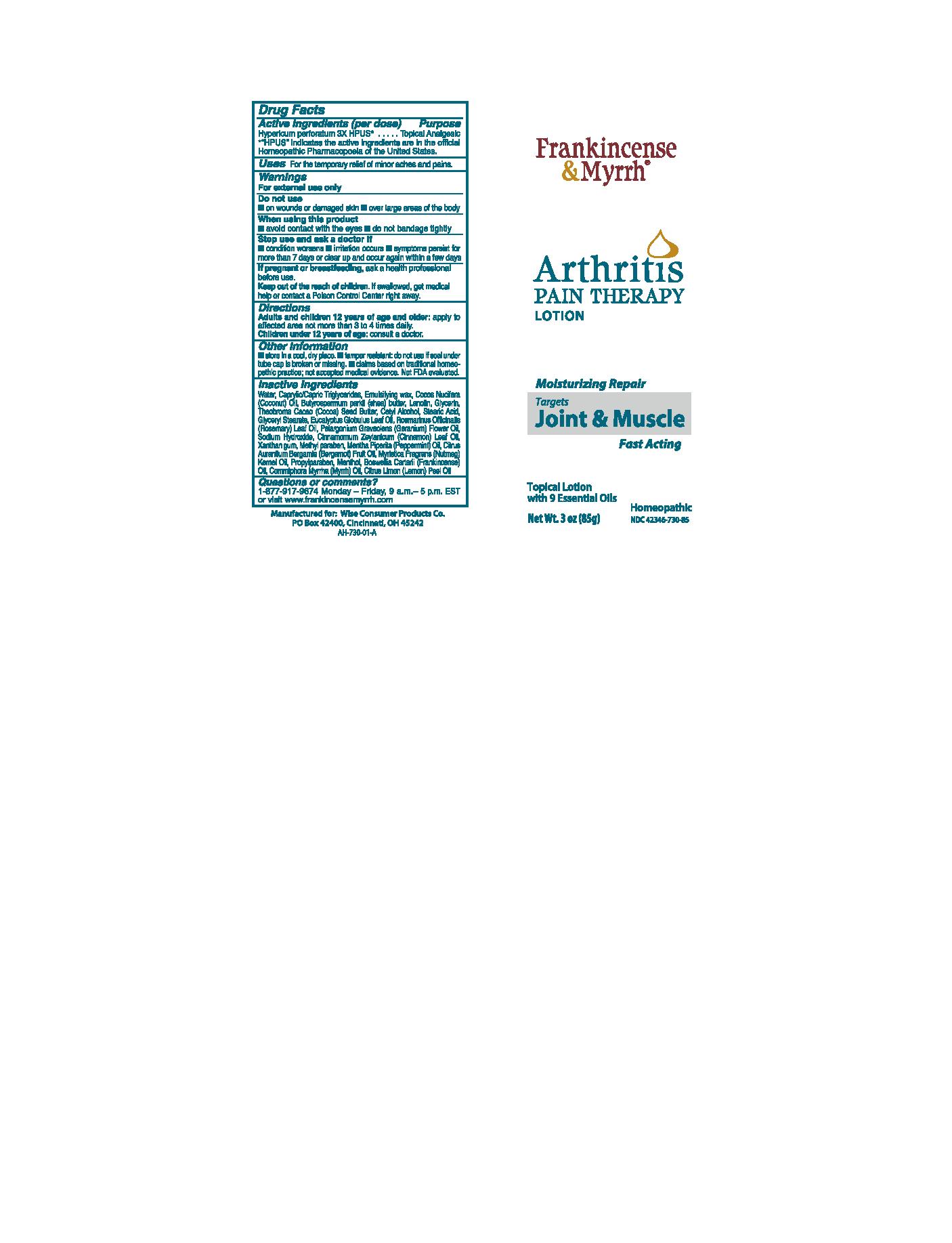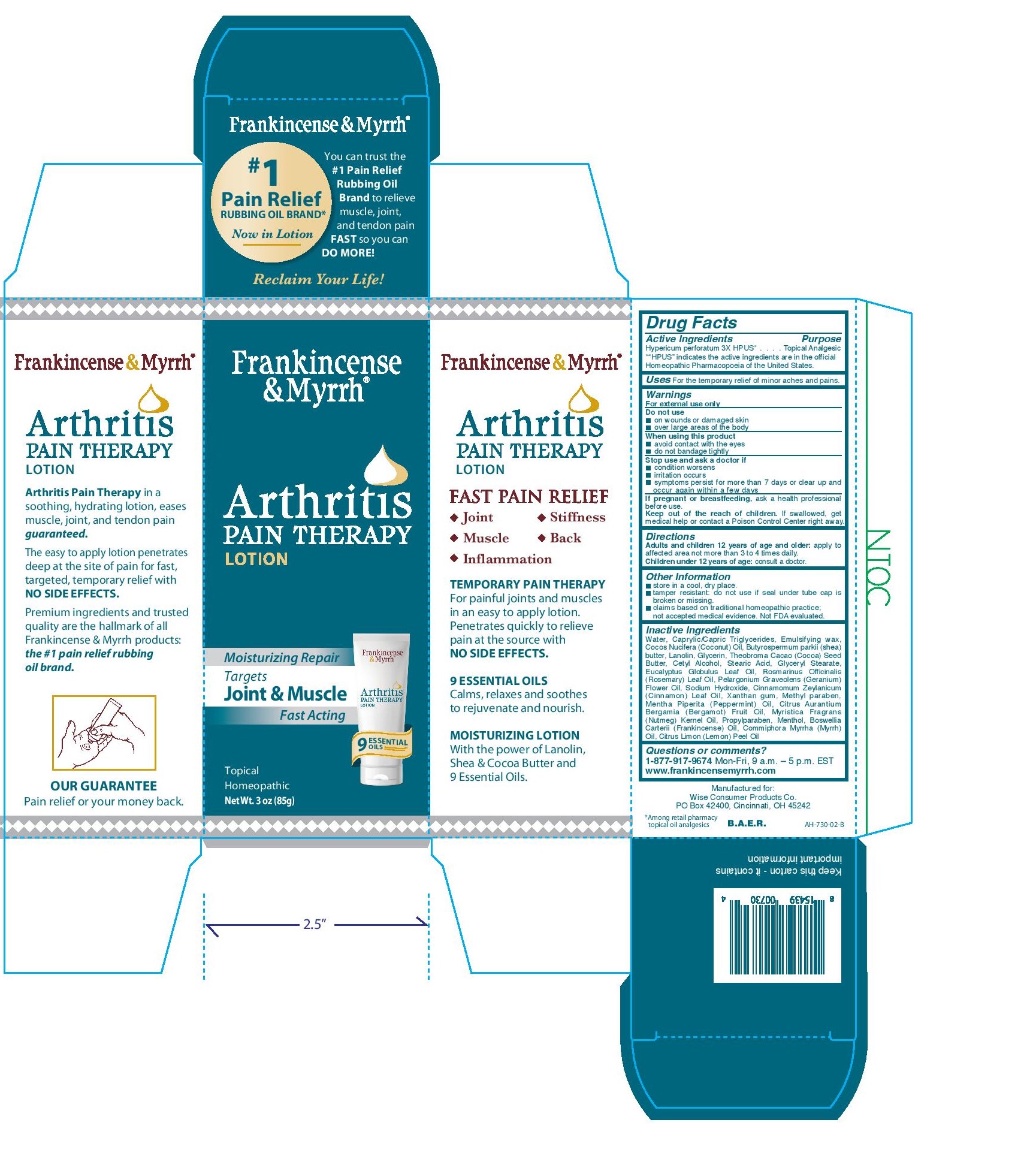 DRUG LABEL: Frankincense and Myrrh Arthritis Pain Therapy
NDC: 42346-730 | Form: LOTION
Manufacturer: Wise Consumer Products Co.
Category: homeopathic | Type: HUMAN OTC DRUG LABEL
Date: 20251231

ACTIVE INGREDIENTS: HYPERICUM PERFORATUM 3 [hp_X]/85 g
INACTIVE INGREDIENTS: COCONUT OIL; GLYCERIN; COCOA BUTTER; CETOSTEARYL ALCOHOL; GLYCERYL MONOSTEARATE; EUCALYPTUS OIL; ROSEMARY OIL; PELARGONIUM GRAVEOLENS FLOWER OIL; SODIUM HYDROXIDE; CINNAMON OIL; METHYLPARABEN; BERGAMOT OIL; NUTMEG OIL; MENTHOL; MYRRH OIL; LEMON OIL; MEDIUM-CHAIN TRIGLYCERIDES; STEARIC ACID; PEPPERMINT OIL; PROPYLPARABEN; FRANKINCENSE OIL; LANOLIN; XANTHAN GUM; SHEA BUTTER; WATER

Frankincense and Myrrh Arthritis Pain Therapy Lotion

Active ingredients

Hypericum perforatum 3X HPUS*

Purpose

Hypericum perforatum 3X HPUS*........Topical Analgesic

*"HPUS" indicates the active ingredients are in the official Homeopathic Pharmacopoeia of the United States.

Uses

For the temporary relief of minor aches and pains.

Warnings

For external use only

Do not use

- on wounds or damaged skin
- over large areas of the body

When using this product

- avoid contact with the eyes
- do not bandage tightly

Stop use and ask a doctor

- if condition worsens
- if irritation occurs
- if symptoms persist for more than 7 days or clear up and occur again within a few days

PREGNANCY OR BREAST FEEDING

If pregnant or breastfeeding, ask a health professional before use.

KEEP OUT OF REACH OF CHILDREN

Keep out of the reach of children. If swallowed, get medical help or contact a Poison Control Center right away.

Directions

Adults and children 12 years of age and older: apply to affected area not more than 3 to 4 times daily.

Children under 12 years of age: consult a doctor.

Other information

- store in a cool, dry place.
- tamper resistant: do not use if seal under tube cap is broken or missing.
- claims based on traditional homeopathc practice; not accepted mediacl evidence. Not FDA evaluated.

Inactive Ingredients

Water, Caprylic/Capric Triglycerides, Emulsifying wax, Cocos Nucifera (Coconut) Oil, Butyrospermum parkii (shea) butter, Lanolin, Glycerin, Theobroma Cacao (Cocoa) Seed Butter, Cetyl Alcohol, Stearic Acid, Glyceryl Stearate, Eucalyptus Globulus Leaf Oil, Rosmarinus Officinalis (Rosemary) Leaf Oil, Pelargonium Graveolens (Geranium) Flower Oil, Sodium Hydroxide, Cinnamomum Zeylanicum (Cinnamon) Leaf Oil, Xanthan gum, Methyl paraben, Mentha Piperita (Peppermint) Oil, Citrus Aurantium Bergamia (Bergamot) Fruit Oil, Myristica Fragrans (Nutmeg) Kernel Oil, Propylparaben, Menthol, Boswellia Carterii (Frankincense) Oil, Commiphora Myrrha (Myrrh) Oil, Citrus Limon (Lemon) Peel Oil

Questions or comments?

1-877-917-9674 Mon-Fri, 9 a.m. - 5 p.m. EST

www.frankincensemyrrh.com

PACKAGE LABEL

Frankincense & Myrrh

Arthritis Pain Therapy Lotion

Moisturizing Repair

Targets Joint & Muscle

Fast-Acting

9 Essential Oils

Homeopathic

Net wt. 3 oz (85g)